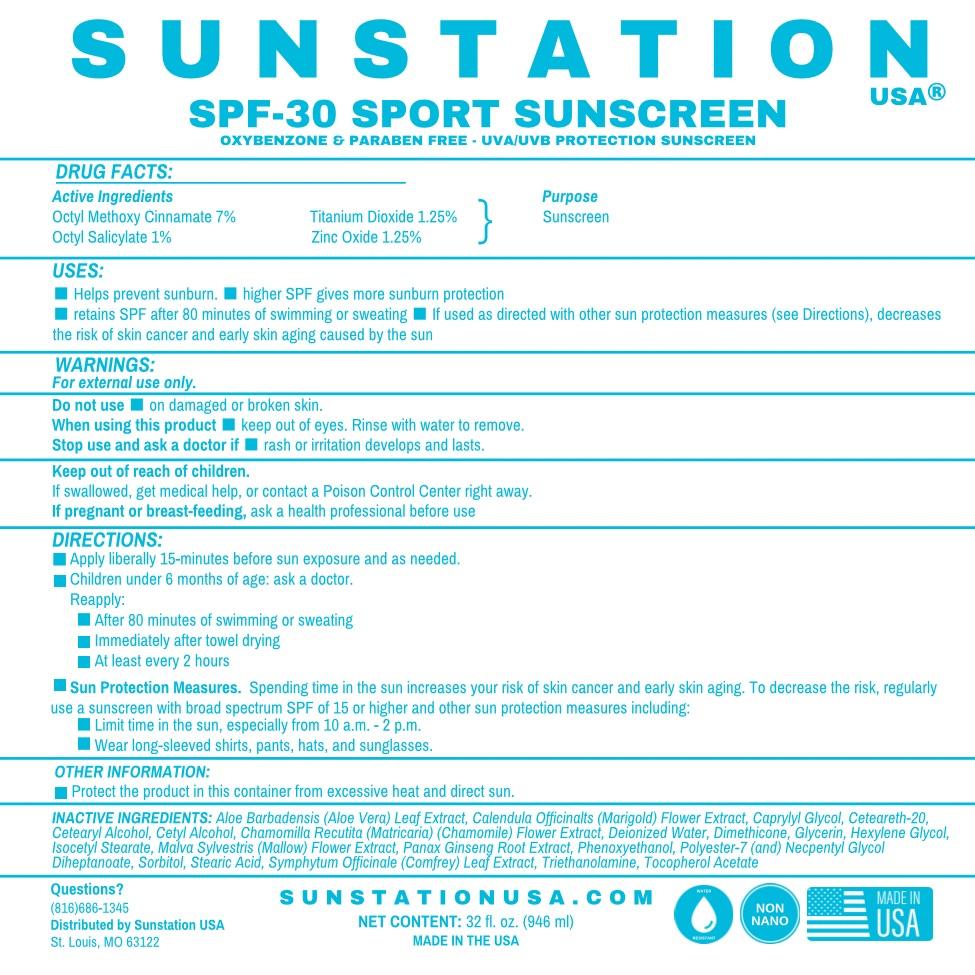 DRUG LABEL: SunStation USA SPF-30 SPORT SUNSCREEN
NDC: 76348-407 | Form: LOTION
Manufacturer: RENU LABORATORIES, LLC
Category: otc | Type: HUMAN OTC DRUG LABEL
Date: 20250131

ACTIVE INGREDIENTS: OCTINOXATE 63 g/896 g; OCTISALATE 9 g/896 g; TITANIUM DIOXIDE 11.2 g/896 g; ZINC OXIDE 11.2 g/896 g
INACTIVE INGREDIENTS: CETOSTEARYL ALCOHOL; DIMETHICONE 350; WATER; ISOCETYL STEARATE; ALPHA-TOCOPHEROL ACETATE; TROLAMINE; ALOE VERA LEAF; POLYESTER-7; NEOPENTYL GLYCOL DIHEPTANOATE; CAPRYLYL GLYCOL; PHENOXYETHANOL; HEXYLENE GLYCOL; STEARIC ACID; CALENDULA OFFICINALIS FLOWER; ASIAN GINSENG; MALVA SYLVESTRIS FLOWER; GLYCERIN; CETYL ALCOHOL; MATRICARIA RECUTITA FLOWERING TOP; COMFREY LEAF; SORBITOL; POLYOXYL 20 CETOSTEARYL ETHER

SUNSTATION USA SPF-30 SPORT SUNSCREEN

Active Ingredients

Octyl Methoxy Cinnamate 7.00% Sunscreen

Titanium Dioxide 1.25% Sunscreen

Zinc Oxide 1.25% Sunscreen

Octyl Salicylate 1.00% Sunscreen

Purpose

Octyl Methoxy Cinnamate 7.00% Sunscreen

Titanium Dioxide 1.25% Sunscreen

Zinc Oxide 1.25% Sunscreen

Octyl Salicylate 1.00% Sunscreen

USES

- Helps prevent sunburn.
- higher SPF gives more sunburn protection
- retains SPF after 80 minutes of swimming or sweating
- If used as directed with other sun protection measures (see Directions), decreases the risk of cancer and early skin aging caused by the sun.

WARNINGS

- For external use only.
- DO NOT USE on damaged or broken skin.
- When using this product keep out of eyes. Rinse with water to remove.
- Stop use and ask a doctor if rash or irritation develops and lasts
- Keep out of reach of children.
- If swallowed, get medical help, or contact a Poison Control Center right away.
- If pregnant or breast-feeding, ask a health professional before use.

DIRECTIONS

- Apply liberally 15 minutes before sun exposure and as needed.
- Children under 6 months of age: ask a doctor.
- After 80 minutes of swimming or sweating.
- Immediately after towel drying.
- At least every 2 hours.
- Sun Protection Measures - Spending time in the sun increases your risk of skin cancer and early skin aging. To decrease this risk, regularly use a sunscreen with broad spectrum SPF of 15 or higher and other sun protection measures including:
- Limit time in the sun, especially between 10am and 2pm.
- Wear long sleeve shirts, pants, hats and sunglasses.

OTHER INGREDIENTS

Aloe Barbadensis (Aloe Vera) Leaf Juice, Calendula Officinalis (Marigold) Flower Extract, Caprylyl Glycol, Ceteareth-20, Cetearyl Alcohol, Deionized Water, Dimethicone, Glycerin, Hexylene Glycol, Isocetyl Stearate, Malva Sylvestris (Mallow) Flower Extract, Panax Ginseng Root Extract, Phenoxyethanol, Polyester-7, Neopentyl Glycol, Diheptanoate, Sorbitol, Stearic Acid,

Symphytum Officinale (Comfrey) Leaf Extract, Triethanolamine, Tocopheryl Acetate (Vitamin E)

- added more descriptive text. No major change.
- Changes to Directions are not major - just a reordering of phrases.

STATEMENT OF IDENTITY

SUNSTATION USA®

SPF-30 SPORT SUNSCREEN

OXYBENZONE & PARABEN FREE

UVA/UVB PROTECTION SUNSCREEN

Keep out of reach of children.
If swallowed, get medical help, or contact a Poison Control Center right away.

OTHER SAFETY INFORMATION

Protect the product in this container from excessive heat and direct sun

QUESTIONS ?

816-686-1345